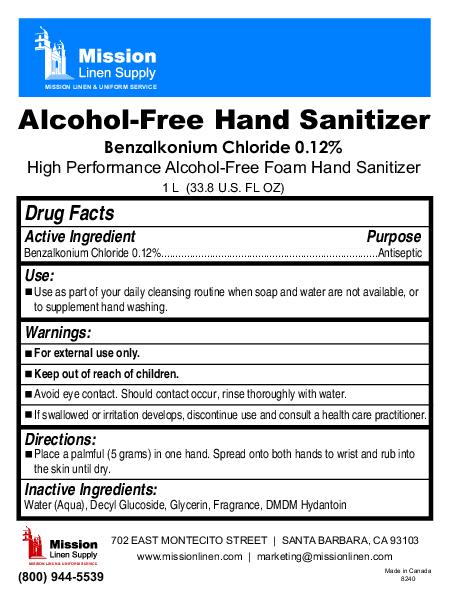 DRUG LABEL: Alcohol free hand sanitizer
NDC: 51053-500 | Form: AEROSOL, FOAM
Manufacturer: Sanihealth Products Corporation
Category: otc | Type: HUMAN OTC DRUG LABEL
Date: 20100524

ACTIVE INGREDIENTS: BENZALKONIUM CHLORIDE 1.2 mL/1000 mL

Alcohol free hand sanitizer

Directions

Place a palmful (5 grams) in one hand. Spread onto both hands to wrist and rub into the skin until dry.

INACTIVE INGREDIENT

Water (Aqua), Decyl Glucoside, Glycerin, Fragrance, DMDM Hydantoin

Warnings:

For external use only.

Keep out of reach of children.

Avoid eye contact. Should contact occur, rinse thoroughly with water.

If swallowed or irritation develops, discontinue use and consult a health care practitioner.

Use

Use as part of your daily cleansing routine when soap and water are not available, or to supplement hand washing.

Active Ingredient Purpose

Benzalkonium Chloride 0.12% Antiseptic

PACKAGE LABEL

Mission Linen supply

Mission linen and uniform service

Alcohol free hand sanitizer

benzalkonium chloride 0.12%

High performance alcohol free foam hand sanitizer

1 L (33.8 U.S. OZ)